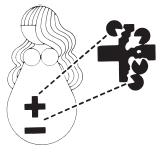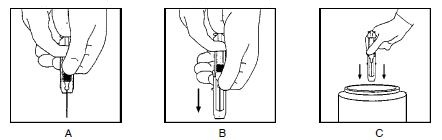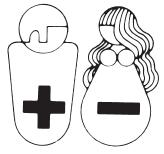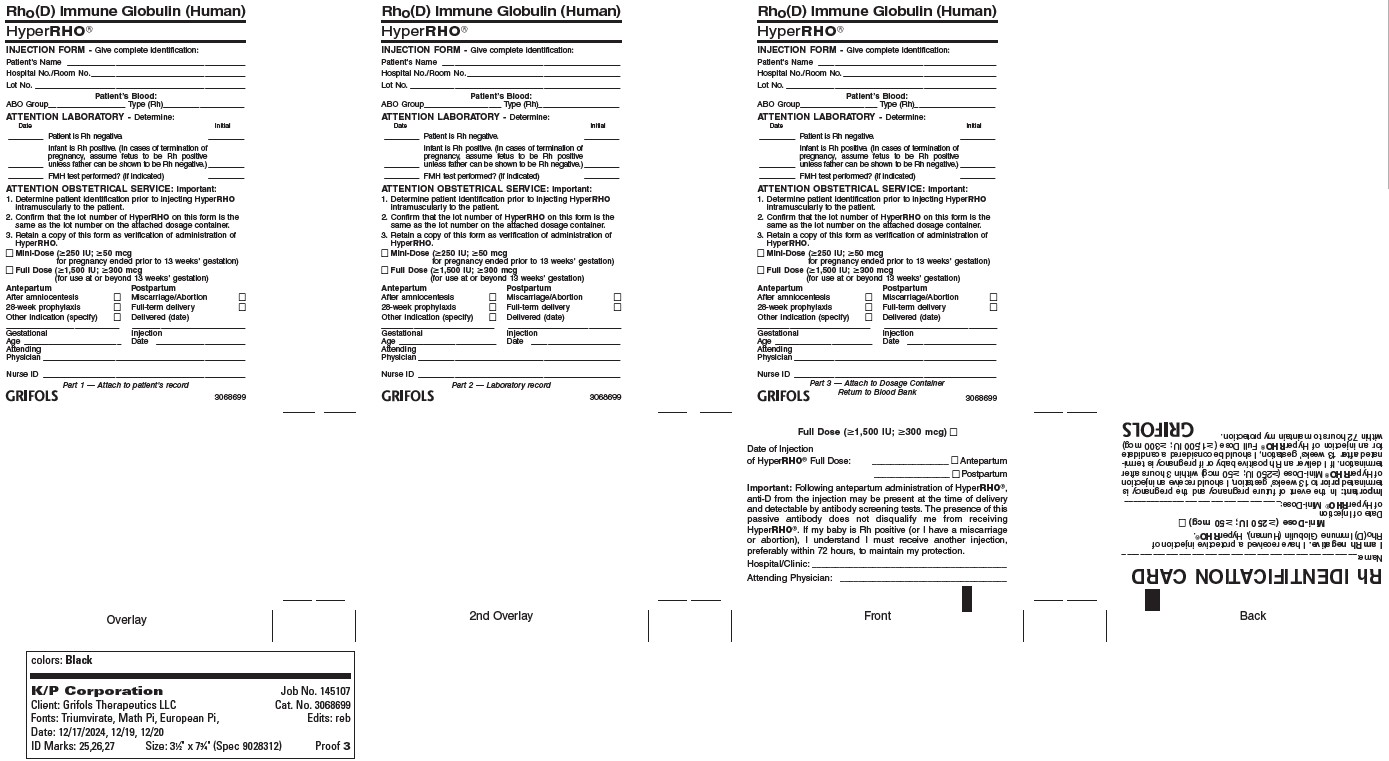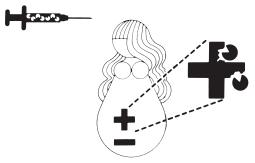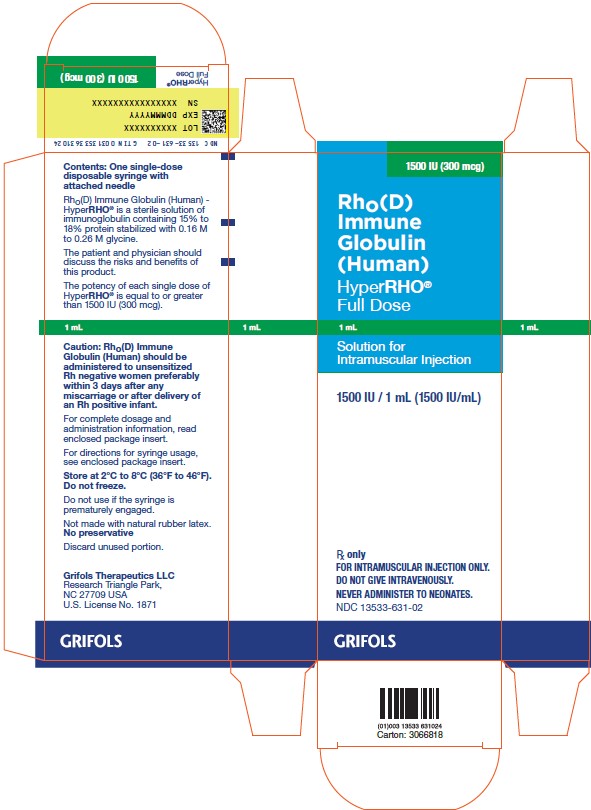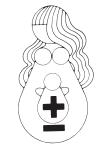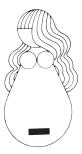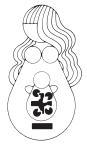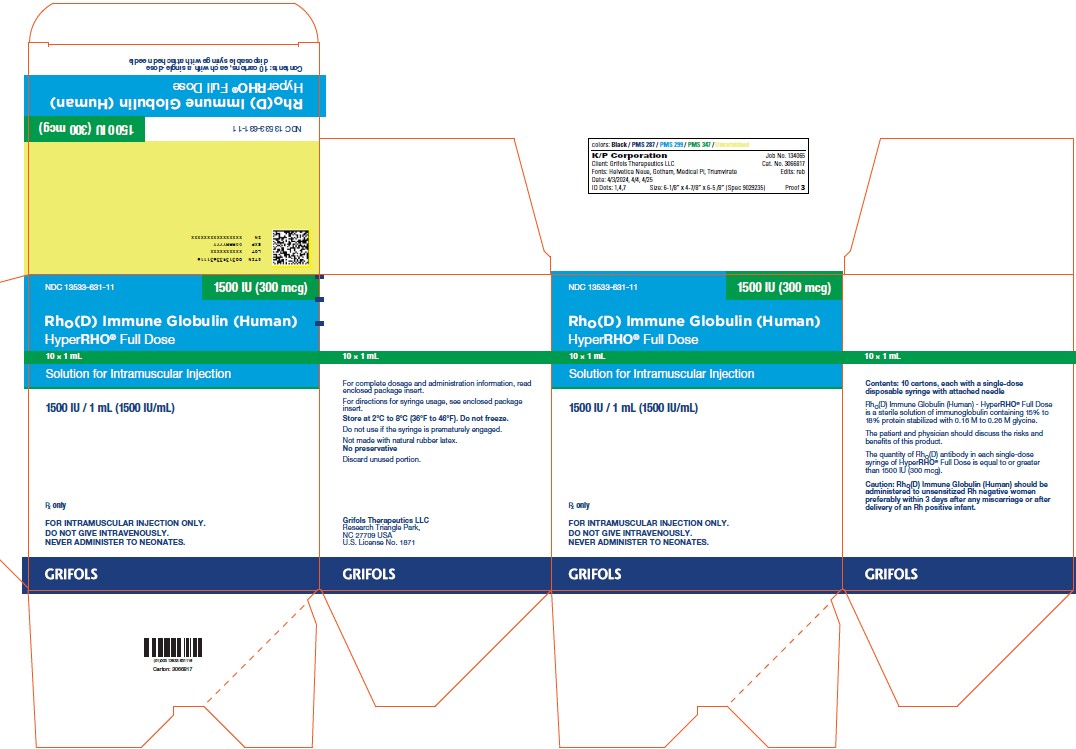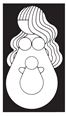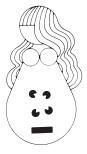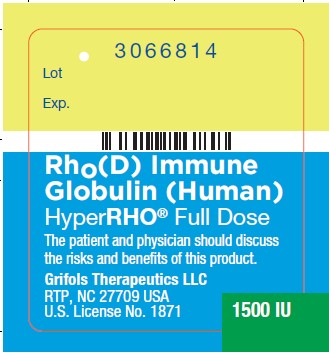 DRUG LABEL: HYPERRHO 
NDC: 13533-631 | Form: SOLUTION
Manufacturer: GRIFOLS USA, LLC
Category: other | Type: PLASMA DERIVATIVE
Date: 20250624

ACTIVE INGREDIENTS: Human Rho(d) Immune Globulin 1500 [iU]/1 mL
INACTIVE INGREDIENTS: Glycine; Water

Rho(D) Immune Globulin (Human)
HyperRHO® Full Dose

DESCRIPTION

Rho(D) Immune Globulin (Human) — HyperRHO® Full Dose is a clear or slightly opalescent and, colorless or pale yellow sterile solution of human rho(D) immune globulin containing antibodies to Rho(D) for intramuscular administration; it contains no preservative. HyperRHO Full Dose is prepared from pools of human plasma collected from healthy donors by a combination of cold ethanol fractionation, caprylate precipitation and filtration, caprylate incubation, anion exchange chromatography, nanofiltration and low pH incubation. HyperRHO Full Dose is formulated as a 15% to 18% protein solution at a pH of 4.1 to 4.8 in 0.16 M to 0.26 M glycine. The potency is equal to or greater than 1500 IU (300 mcg) per 1 mL. Each single-dose syringe contains sufficient anti-Rho(D) to effectively suppress the immunizing potential of 15 mL of Rho(D) positive red blood cells.(1-4)

When medicinal biological products are administered, the risk of infectious diseases due to transmission of pathogens cannot be totally excluded. However, in the case of products prepared from human plasma, the risk of transmission of pathogens is reduced by epidemiological surveillance of the donor population and selection of individual donors by medical interview; testing of individual donations and plasma pools; and the presence in the manufacturing processes of steps with demonstrated capacity to inactivate/remove pathogen.

In the manufacturing process of HyperRHO Full Dose, there are several steps with the capacity for viral inactivation or removal.(5) The main steps of the manufacturing process that contribute to the virus clearance capacity are as follows:

- Caprylate precipitation/depth filtration
- Caprylate incubation
- Depth filtration
- Column chromatography
- Nanofiltration
- Low pH final container incubation

To provide additional assurance of the pathogen safety of the final product, the capacity of the HyperRHO Full Dose manufacturing process to remove and/or inactivate viruses has been demonstrated by laboratory spiking studies on a scaled down process model using a wide range of viruses with diverse physicochemical properties.

The combination of all of the above-mentioned measures provides the final product with a high margin of safety from the potential risk of transmission of infectious viruses.

The caprylate/chromatography manufacturing process was also investigated for its capacity to decrease the infectivity of an experimental agent of transmissible spongiform encephalopathy (TSE), considered as a model for the variant Creutzfeldt-Jakob disease (vCJD) and Creutzfeldt-Jakob disease (CJD) agents.(5) These studies provide reasonable assurance that low levels of CJD/vCJD agent infectivity, if present in the starting material, would be removed by the caprylate/chromatography manufacturing process.

CLINICAL PHARMACOLOGY

HyperRHO Full Dose is used to prevent isoimmunization in the Rho(D) negative individual exposed to Rho(D) positive blood as a result of a fetomaternal hemorrhage occurring during a delivery of an Rho(D) positive infant, abortion (either spontaneous or induced), or following amniocentesis or abdominal trauma. Similarly, immunization resulting in the production of anti-Rho(D) following transfusion of Rh positive red cells to an Rho(D) negative recipient may be prevented by administering Rho(D) Immune Globulin (Human).(6,7)

Rh hemolytic disease of the newborn is the result of the active immunization of an Rho(D) negative mother by Rho(D) positive red cells entering the maternal circulation during a previous delivery, abortion, amniocentesis, abdominal trauma, or as a result of red cell transfusion.(8,9) HyperRHO Full Dose acts by suppressing the immune response of Rho(D) negative individuals to Rho(D) positive red blood cells. The mechanism of action of HyperRHO Full Dose is not fully understood.

The administration of Rho(D) Immune Globulin (Human) within 72 hours of a full-term delivery of an Rho(D) positive infant by an Rho(D) negative mother reduces the incidence of Rh isoimmunization from 12%–13% to 1%–2%.(10)

The 1%–2% treatment failures are probably due to isoimmunization occurring during the latter part of pregnancy or following delivery.(11) Bowman and Pollock(12) have reported that the incidence of isoimmunization can be further reduced from approximately 1.6% to less than 0.1% by administering Rho(D) Immune Globulin (Human) in two doses, one antenatal at 28 weeks’ gestation and another following delivery.

In a clinical study in 12 healthy human adults receiving another hyperimmune immune globulin product, Rabies Immune Globulin (Human), HyperRAB®, prepared by the same manufacturing process, detectable passive antibody titers were observed in the serum of all subjects by 24 hours post injection and persisted through the 21 day study period.

INDICATIONS AND USAGE

Pregnancy and Other Obstetric Conditions

HyperRHO Full Dose is recommended for the prevention of Rh hemolytic disease of the newborn by its administration to the Rho(D) negative mother within 72 hours after birth of an Rho(D) positive infant,(13) providing the following criteria are met:

1. The mother must be Rho(D) negative and must not already be sensitized to the Rho(D) factor.
2. Her child must be Rho(D) positive, and should have a negative direct antiglobulin test (see PRECAUTIONS).

If HyperRHO Full Dose is administered antepartum, it is essential that the mother receive another dose of HyperRHO Full Dose after delivery of an Rho(D) positive infant.

If the father can be determined to be Rho(D) negative, HyperRHO Full Dose need not be given.

HyperRHO Full Dose should be administered within 72 hours to all nonimmunized Rho(D) negative women who have undergone spontaneous or induced abortion, following ruptured tubal pregnancy, amniocentesis or abdominal trauma unless the blood group of the fetus or the father is known to be Rho(D) negative.(8,9) If the fetal blood group cannot be determined, one must assume that it is Rho(D) positive,(2) and HyperRHO Full Dose should be administered to the mother.

Transfusion

HyperRHO Full Dose may be used to prevent isoimmunization in Rho(D) negative individuals who have been transfused with Rho(D) positive red blood cells or blood components containing red blood cells.(6,14)

CONTRAINDICATIONS

None known.

WARNINGS

HyperRHO Full Dose is made from human plasma. Products made from human plasma may contain infectious agents, such as viruses, the variant Creutzfeldt-Jakob disease (vCJD) agent, and, theoretically, the Creutzfeldt-Jakob Disease (CJD) agent that can cause disease. The risk that such products will transmit an infectious agent has been reduced by screening plasma donors for prior exposure to certain viruses, by testing for the presence of certain current virus infections, and by including manufacturing steps that inactivate and/or remove viruses. Despite these measures, such products can still potentially transmit disease. There is also the possibility that unknown infectious agents may be present in such products. Individuals who receive infusions of blood or plasma products may develop signs and/or symptoms of some viral infections, particularly hepatitis C. ALL infections thought by a physician possibly to have been transmitted by this product should be reported by the physician or other healthcare provider to Grifols Therapeutics LLC [1-800-520-2807].

The physician should discuss the risks and benefits of this product with the patient, before prescribing or administering it to the patient.

NEVER ADMINISTER HYPERRHO FULL DOSE INTRAVENOUSLY. INJECT ONLY INTRAMUSCULARLY. NEVER ADMINISTER TO THE NEONATE.

Rho(D) Immune Globulin (Human) should be given with caution to patients with a history of prior systemic allergic reactions following the administration of human immunoglobulin preparations.

The attending physician who wishes to administer Rho(D) Immune Globulin (Human) to persons with isolated immunoglobulin A (IgA) deficiency must weigh the benefits of immunization against the potential risks of hypersensitivity reactions. Such persons have increased potential for developing antibodies to IgA and could have anaphylactic reactions to subsequent administration of blood products that contain IgA.

As with all preparations administered by the intramuscular route, bleeding complications may be encountered in patients with thrombocytopenia or other bleeding disorders.

PRECAUTIONS

General

A large fetomaternal hemorrhage late in pregnancy or following delivery may cause a weak mixed field positive Du test result. If there is any doubt about the mother’s Rh type, she should be given Rho(D) Immune Globulin (Human). A screening test to detect fetal red blood cells may be helpful in such cases.

If more than 15 mL of D-positive fetal red blood cells are present in the mother’s circulation, more than a single dose of HyperRHO Full Dose is required. Failure to recognize this may result in the administration of an inadequate dose.

Although systemic reactions to human immunoglobulin preparations are rare, epinephrine should be available for treatment of acute anaphylactic reactions.

Drug Interactions

Other antibodies in the Rho(D) Immune Globulin (Human) preparation may interfere with the response to live vaccines such as measles, mumps, polio or rubella. Therefore, immunization with live vaccines should not be given within 3 months after Rho(D) Immune Globulin (Human) administration.

Drug/Laboratory Interactions

Babies born of women given Rho(D) Immune Globulin (Human) antepartum may have a weakly positive direct antiglobulin test at birth.

Passively acquired anti-Rho(D) may be detected in maternal serum if antibody screening tests are performed subsequent to antepartum or postpartum administration of Rho(D) Immune Globulin (Human).

Pregnancy

Animal reproduction studies have not been conducted with Rho(D) Immune Globulin (Human) — HyperRHO® Full Dose. It is also not known whether HyperRHO Full Dose can cause fetal harm when administered to a pregnant woman or can affect reproduction capacity. HyperRHO Full Dose should be given to a pregnant woman only if clearly needed.

Pediatric Use

Safety and effectiveness in the pediatric population have not been established.

ADVERSE REACTIONS

Reactions to Rho(D) Immune Globulin (Human) are infrequent in Rho(D) negative individuals and consist primarily of slight soreness at the site of injection and slight temperature elevation. While sensitization to repeated injections of human immune globulin is extremely rare, it has occurred. Elevated bilirubin levels have been reported in some individuals receiving multiple doses of Rho(D) Immune Globulin (Human) following mismatched transfusions. This is believed to be due to a relatively rapid rate of foreign red cell destruction.

DOSAGE AND ADMINISTRATION

NEVER ADMINISTER HYPERRHO FULL DOSE INTRAVENOUSLY. INJECT ONLY INTRAMUSCULARLY. NEVER ADMINISTER TO THE NEONATE.

Pregnancy and Other Obstetric Conditions

1. For postpartum prophylaxis, administer one syringe of HyperRHO Full Dose (1500 IU; 300 mcg), preferably within 72 hours of delivery. Although a lesser degree of protection is afforded if Rh antibody is administered beyond the 72-hour period, HyperRHO Full Dose may still be given.(8,15) Full-term deliveries can vary in their dosage requirements depending on the magnitude of the fetomaternal hemorrhage. One full dose syringe of HyperRHO Full Dose provides sufficient antibody to prevent Rh sensitization if the volume of red blood cells that has entered the circulation is 15 mL or less.(2-4) In instances where a large (greater than 30 mL of whole blood or 15 mL red blood cells) fetomaternal hemorrhage is suspected, a fetal red cell count by an approved laboratory technique (e.g., modified Kleihauer-Betke acid elution stain technique) should be performed to determine the dosage of immune globulin required.(9,16) The red blood cell volume of the calculated fetomaternal hemorrhage is divided by 15 mL to obtain the number of syringes of HyperRHO Full Dose (1500 IU; 300 mcg) for administration.(3,9,14) If more than 15 mL of red cells is suspected or if the dose calculation results in a fraction, administer the next higher whole number of syringes (e.g., if 1.4, give 2 syringes).
2. For antenatal prophylaxis, one full dose syringe of HyperRHO Full Dose (1500 IU; 300 mcg) is administered at approximately 28 weeks’ gestation. This must be followed by another full dose (1500 IU; 300 mcg), preferably within 72 hours following delivery, if the infant is Rh positive.
3. Following threatened abortion at any stage of gestation with continuation of pregnancy, it is recommended that a full dose of HyperRHO Full Dose (1500 IU; 300 mcg) be given. If more than 15 mL of red cells is suspected due to fetomaternal hemorrhage, the same dose modification in No. 1 above applies.
4. Following miscarriage, abortion, or termination of ectopic pregnancy at or beyond 13 weeks’ gestation, it is recommended that a HyperRHO Full Dose (1500 IU; 300 mcg) be given. If more than 15 mL of red cells is suspected due to fetomaternal hemorrhage, the same dose modification in No. 1 above applies. If pregnancy is terminated prior to 13 weeks’ gestation, where licensed, a single dose of HyperRHO® Mini-Dose (250 IU; 50 mcg) may be used instead of HyperRHO Full Dose (1500 IU; 300 mcg).
5. Following amniocentesis at either 15 to 18 weeks’ gestation or during the third trimester, or following abdominal trauma in the second or third trimester, it is recommended that a HyperRHO Full Dose (1500 IU; 300 mcg) be administered. If there is a fetomaternal hemorrhage in excess of 15 mL of red cells, the same dose modification in No. 1 applies.

If abdominal trauma, amniocentesis, or other adverse event requires the administration of HyperRHO Full Dose (1500 IU; 300 mcg) at 13 to 18 weeks’ gestation, another full dose should be given at 26 to 28 weeks. To maintain protection throughout pregnancy, the level of passively acquired anti-Rho(D) should not be allowed to fall below the level required to prevent an immune response to Rh positive red cells. The half-life of IgG is 23 to 26 days. In any case, a HyperRHO Full Dose should be given within 72 hours after delivery if the baby is Rh positive. If delivery occurs within 3 weeks after the last dose, the postpartum dose may be withheld unless there is a fetomaternal hemorrhage in excess of 15 mL of red blood cells.(17)

Transfusion

In the case of a transfusion of Rho(D) positive red cells to an Rho(D) negative recipient, the volume of Rh positive whole blood administered is multiplied by the hematocrit of the donor unit giving the volume of red blood cells transfused. The volume of red blood cells is divided by 15 mL which provides the number of syringes of HyperRHO Full Dose to be administered.

If the dose calculated results in a fraction, the next higher whole number of syringes should be administered (e.g., if 1.4, give 2 syringes). HyperRHO Full Dose should be administered within 72 hours after an incompatible transfusion, but preferably as soon as possible.

Injection Procedure

DO NOT INJECT INTRAVENOUSLY. DO NOT INJECT NEONATE. HyperRHO Full Dose is administered intramuscularly, preferably in the deltoid muscle of the upper arm or lateral thigh muscle. The gluteal region should not be used as an injection site because of the risk of injury to the sciatic nerve.(18)

A. Single Syringe Dose
INJECT ENTIRE CONTENTS OF THE SYRINGE INTO THE INDIVIDUAL INTRAMUSCULARLY.
B. Multiple Syringe Dose

1. Calculate the number of syringes of HyperRHO Full Dose to be given (see Dosage section).
2. The total volume of HyperRHO Full Dose can be given in divided doses at different sites at one time or the total dose may be divided and injected at intervals, provided the total dosage is given within 72 hours of the fetomaternal hemorrhage or transfusion. USING STERILE TECHNIQUE, INJECT THE ENTIRE CONTENTS OF THE CALCULATED NUMBER OF SYRINGES INTRAMUSCULARLY INTO THE PATIENT.

Parenteral drug products should be inspected visually for particulate matter and discoloration prior to administration, whenever solution and container permit.

HyperRHO Full Dose is supplied with a syringe and an attached needle guard for your protection and convenience. Please follow instructions below for proper use of syringe and needle guard.

Directions for Syringe Usage

1. Remove the prefilled syringe from the package. Lift syringe by barrel, not by plunger.
2. Twist the plunger rod clockwise until the threads are seated. Do not use if the syringe is prematurely engaged.
3. With the rubber needle shield secured on the syringe tip, push the plunger rod forward a few millimeters to break any friction seal between the rubber stopper and the glass syringe barrel.
4. Remove the needle shield and expel air bubbles. [Do not remove the rubber needle shield to prepare the product for administration until immediately prior to the anticipated injection time.]
5. Proceed with hypodermic needle puncture.
6. Aspirate prior to injection to confirm that the needle is not in a vein or artery.
7. Inject the medication.
8. Keeping your hands behind the needle, grasp the guard with free hand and slide forward toward needle until it is completely covered and guard clicks into place. If audible click is not heard, guard may not be completely activated. (See Diagrams A and B)
9. Place entire prefilled glass syringe with guard activated into an approved sharps container for proper disposal. (See Diagram C)

A number of factors could reduce the efficacy of this product or even result in an ill effect following its use. These include improper storage and handling of the product after it leaves our hands, diagnosis, dosage, method of administration, and biological differences in individual patients. Because of these factors, it is important that this product be stored properly and that the directions be followed carefully during use.

HOW SUPPLIED

HyperRHO Full Dose is available in a single-dose syringe with attached needle. HyperRHO Full Dose is packaged as 1 syringe per carton, and as 10 cartons each with a single dose disposable syringe. HyperRHO Full Dose contains no preservative and is not made with natural rubber latex.

NDC Number | Size
13533-631-02 | Syringe
13533-631-11 | Syringe (10 Pack)

STORAGE

Store at 2°C to 8°C (36°F to 46°F). Do not freeze. Do not use after expiration date. Discard unused portion.

CAUTION

Rx only
U.S. federal law prohibits dispensing without prescription.

REFERENCES

1. Gunson HH, Bowell PJ, Kirkwood TBL: Collaborative study to recalibrate the International Reference Preparation of Anti-D Immunoglobulin. J Clin Pathol 33:249-53, 1980.
2. Rho(D) immune globulin (human). Med Lett Drugs Ther 16(1):3-4, 1974.
3. Pollack W, Ascari WQ, Kochesky RJ, et al: Studies on Rh prophylaxis. I. Relationship between doses of anti-Rh and size of antigenic stimulus. Transfusion 11(6):333-9, 1971.
4. Unpublished data on file.
5. Barnette D, Roth NJ, Hotta J, et al. Pathogen safety profile of a 10% IgG preparation manufactured using a depth filtration-modified process. Biologicals 2012;40:247-53.
6. Pollack W, Ascari WQ, Crispen JF, et al: Studies on Rh prophylaxis. II. Rh immune prophylaxis after transfusion with Rh-positive blood. Transfusion 11(6):340-4, 1971.
7. Keith LG, Houser GH: Anti-Rh immune globulin after a massive transfusion accident. Transfusion 11(3):176, 1971.
8. The selective use of Rho(D) immune globulin (RhIG). ACOG Tech Bull 61, 1981.
9. Current uses of Rho immune globulin and detection of antibodies. ACOG Tech Bull 35, 1976.
10. Pollack W: Rh hemolytic disease of the newborn: its cause and prevention. Prog Clin Biol Res 70:185-203, 1981.
11. Bowman JM, Chown B, Lewis M, et al: Rh isoimmunization during pregnancy: antenatal prophylaxis. Can Med Assoc J 118(6):623-7, 1978.
12. Bowman JM, Pollock JM: Antenatal prophylaxis of Rh isoimmunization: 28-weeks'- gestation service program. Can Med Assoc J 118(6):627-30, 1978.
13. Ascari WQ, Allen AE, Baker WJ, et al: Rho(D) immune globulin (human): evaluation in women at risk of Rh immunization. JAMA 205(1):1-4, 1968.
14. Prevention of Rh sensitization. WHO Tech Rep Ser 468:25, 1971.
15. Samson D, Mollison PL: Effect on primary Rh immunization of delayed administration of anti-Rh. Immunology 28:349-57, 1975.
16. Finn R, Harper DT, Stallings SA, et al: Transplacental hemorrhage. Transfusion 3(2):114-24, 1963.
17. Garraty G (ed.): Hemolytic disease of the newborn. Arlington, VA, American Association of Blood Banks, 1984, p 78.
18. Recommendations of the Advisory Committee on Immunization Practices (ACIP) and the American Academy of Family Physicians (AAFP): General recommendations on immunization. MMWR 2002: 51(RR02), 1-36.

(Rev. 5/2025)
GRIFOLS
Grifols Therapeutics LLC
Research Triangle Park, NC 27709 USA 3068044
U.S. License No. 1871

PATIENT COUNSELING INFORMATION

The Rh Factor and Your Pregnancy

Information About Pregnancy Protection

The Rh Factor and When It Is Important

The Rh factor is one of many blood group antigens found on the surface of red blood cells. If you have this antigen you are considered Rh positive. If you don’t, then you are considered Rh negative. Everyone is either Rh positive or Rh negative. One type is neither better nor worse than the other, only different.

Your Rh factor is important if you are an Rh negative woman and you become pregnant, or if you receive a blood transfusion.

How the Rh Factor Can Affect Your Future

If you have Rh negative blood, there are two situations that can affect you:

1. If the father of your baby is Rh positive, the baby will probably be Rh positive too. An Rh negative woman carrying an Rh positive baby may have an immune reaction if some of the baby’s Rh positive blood cells enter her bloodstream.
This immune reaction, called isoimmunization, means your body’s defense system recognizes Rh positive blood as foreign from your own and produces “antibodies” to destroy the invading Rh positive blood cells.
The passage of blood from the baby to the mother’s bloodstream happens most often at delivery, but can also occur during miscarriage, the termination of pregnancy, amniocentesis (test performed to determine fetal health), or due to an injury or trauma. It is important to note that a small number of women develop antibodies to Rh positive blood cells during pregnancy for no apparent reason.
Antibodies to Rh positive blood may not be a problem in first pregnancies; however, the antibodies stay in your bloodstream, ready to attack invading Rh positive blood cells, for many years to come. This can lead to problems in future pregnancies by causing miscarriage or a disease known as hemolytic disease of the newborn.
Babies born to Rh positive mothers, regardless of the father’s blood type, will usually be free of the dangers of hemolytic disease.
2. Someday it may become necessary for you to receive a blood transfusion. If Rh positive antibodies already reside in your bloodstream due to isoimmunization and the blood you receive is Rh positive due to error or lifesaving reasons, your Rh positive antibodies will become mobilized and destroy the donor Rh positive cells. As a result, the transfusion could be unsuccessful and possibly harmful to you.

Hemolytic Disease of the Newborn: A Threat to Your Baby

When an Rh negative woman has Rh positive antibodies in her blood and the baby she is carrying is Rh positive, the antibodies could possibly enter the baby’s bloodstream, attack the baby’s red blood cells and cause hemolytic disease of the newborn. At birth, the infant suffering from hemolytic disease may be jaundiced and anemic or suffer permanent damage of the brain and central nervous system which may result in mental retardation, hearing loss, or cerebral palsy. Extensive medical care can be required, including an exchange transfusion, in which all of the baby’s blood is replaced. This usually stops the destruction of the baby’s red blood cells and gives the infant a chance to survive.

The risk of hemolytic disease of the newborn is slight with the first baby, but increases with each successive pregnancy.

Preventing Hemolytic Disease

HyperRHO®, Rho(D) Immune Globulin (Human) can prevent hemolytic disease of the newborn, provided Rh positive antibodies do not already reside in your bloodstream.

HyperRHO is a specially prepared gamma globulin with a high level of preformed antibodies against Rh positive blood cells. The injection of HyperRHO destroys any Rh positive blood cells that may have entered the mother’s bloodstream and prevents the mother’s immune system from producing Rh positive antibodies; thus protecting the baby from developing hemolytic disease.

HyperRHO Full Dose — When Prescribed

Pregnancy and Other Obstetric Conditions Pertaining to Rh Negative Women

HyperRHO Full Dose (1500 IU; 300 mcg) is administered during pregnancy if you fall into a high-risk category. For example, you are at risk of producing Rh positive antibodies if you have an amniocentesis procedure performed, or if you have a miscarriage or other termination of pregnancy at or beyond 13 weeks' gestation.

Laboratory findings have shown that some Rh negative women develop Rh positive antibodies during the last weeks of pregnancy even without an antibody-stimulating event. As a preventive measure, your physician will probably recommend the first injection of HyperRHO Full Dose at the 28th week of pregnancy.

In both of the above situations, if the blood type of the father or baby can be determined to be Rh negative, an injection of HyperRHO is not required.

Another injection of HyperRHO Full Dose is administered within 72 hours of delivery of an Rh positive baby.

Blood Transfusion

HyperRHO Full Dose (1500 IU; 300 mcg) may be used to prevent isoimmunization in Rh negative individuals who have been transfused with Rh positive red blood cells or blood components containing red blood cells.

HyperRHO Mini-Dose — When Prescribed

A single dose of HyperRHO Mini-Dose (250 IU; 50 mcg) may be prescribed for an Rh negative woman instead of HyperRHO Full Dose (1500 IU; 300 mcg) in the event of miscarriage or other termination of pregnancy occurring prior to 13 weeks' gestation. HyperRHO Mini-Dose is not required if the blood type of the father or fetus can be determined to be Rh negative.

Will You Need HyperRHO Again?

HyperRHO provides protection only if you have not already produced Rh positive antibodies. Women who have developed antibodies through previous pregnancy, miscarriage, other termination of pregnancy, or blood transfusion cannot be protected by HyperRHO. This is why with each pregnancy it is important to have HyperRHO injections within the prescribed time period.

Reactions to HyperRHO

You may feel a temporary soreness at the site of the injection. You may also have a slight and temporary change in body temperature. In very rare instances, an allergic type of reaction can occur, for which your physician will take appropriate measures.

Delivering a Sound, Healthy Baby

Your physician can answer any questions you may have about receiving a HyperRHO injection to prevent hemolytic disease of the newborn. If you know that you are Rh negative and you are pregnant, you should discuss your situation with your physician. Today, with HyperRHO, hemolytic disease of the newborn can be reduced to its lowest possible rate of incidence.

GRIFOLS
Grifols Therapeutics LLC
Research Triangle Park, NC 27709 USA 3068044
U.S. License No. 1871 (Rev. 5/2025)

Development of Hemolytic Disease

1 Rh positive (+) father. Rh negative (–) mother. | 2 Pregnancy: Rh– mother is carrying Rh+ baby.
3 The passage of Rh+ blood from the baby to the mother's bloodstream happens most often at delivery, but can also occur during miscarriage, other termination of pregnancy, amniocentesis, or due to injury or trauma. | 4 Rh+ antibodies stay in your bloodstream, ready to attack invading Rh+ blood cells, for many years to come.
5 Next pregnancy, mother’s Rh+ antibodies enter baby’s Rh+ bloodstream, attacking baby’s blood cells and causing hemolytic disease of the newborn.

How HyperRHO Immune Globulin Can Prevent Hemolytic Disease

1 You will probably be given two injections of HyperRHO Full Dose, one at the 28th week of your pregnancy and another within 72 hours of delivery, miscarriage or other termination of pregnancy. A single injection of HyperRHO Mini-Dose may be prescribed instead of HyperRHO Full Dose in the event of miscarriage or other termination of pregnancy occurring prior to 13 weeks' gestation. | 2 HyperRHO immunization prevents formation of mother's own Rh+ antibodies. Mother’s bloodstream remains free of Rh+ antibodies.
3 Next pregnancy, baby develops normally. HyperRHO should be administered following delivery, miscarriage, or other termination of pregnancy to continue protection if baby is Rh+.

PACKAGE LABEL

3066814
Lot
Exp.
Rho (D) Immune
Globulin (Human)
HyperRHO® Full Dose
The patient and physician should discuss
the risks and benefits of this product.
Grifols Therapeutics LLC
RTP, NC 27709 USA
U.S. License No. 1871
1500 IU

1500 IU (300 mcg)
Rho (D)
Immune
Globulin
(Human)
HyperRHO®
Full Dose
1 mL
Solution for
Intramuscular Injection
1500 IU / 1 mL (1500 IU/mL)
Rx only
FOR INTRAMUSCULAR INJECTION ONLY.
DO NOT GIVE INTRAVENOUSLY.
NEVER ADMINISTER TO NEONATES.
NDC 13533-631-02
GRIFOLS
Contents: One single-dose
disposable syringe with
attached needle
Rho(D) Immune Globulin (Human) -
HyperRHO® is a sterile solution
of immunoglobulin containing
15% to 18% protein stabilized with
0.16 M to 0.26 M glycine.
The patient and physician should
discuss the risks and benefits of this
product.
The potency of each single dose of
HyperRHO® is equal to or
greater than 1500 IU (300 mcg).
Caution: Rho (D) Immune
Globulin (Human) should be
administered to unsensitized
Rh negative women preferably
within 3 days after any
miscarriage or after delivery of
an Rh positive infant.
For complete dosage and
administration information,
read enclosed package insert.
For directions for syringe usage,
see enclosed package insert.
Store at 2°C to 8°C (36°F to 46°F).
Do not freeze.
Do not use if the syringe is
prematurely engaged.
Not made with natural rubber latex.
No preservative
Discard unused portion.
Grifols Therapeutics LLC
Research Triangle Park,
NC 27709 USA
U.S. License No. 1871
GRIFOLS
NDC 13533-631-02 GTIN 00313533631024
LOT XXXXXXXXXX
EXP DDMMMYYYY
SN XXXXXXXXXXXXXXXX
HyperRHO®
Full Dose
1500 IU (300 mcg)

NDC 13533-631-11
1500 IU (300 mcg)
Rho (D) Immune Globulin (Human)
HyperRHO® Full Dose
10 x 1 mL
Solution for Intramuscular Injection
1500 IU / 1 mL (1500 IU/mL)
Rx only
FOR INTRAMUSCULAR INJECTION ONLY.
DO NOT GIVE INTRAVENOUSLY.
NEVER ADMINISTER TO NEONATES.
GRIFOLS
Contents: 10 cartons, each with a single-dose
disposable syringe with attached needle
Rho(D) Immune Globulin (Human) - HyperRHO® Full Dose
is a sterile solution of immunoglobulin containing 15% to
18% protein stabilized with 0.16 M to 0.26 M glycine.
The patient and physician should discuss the risks and
benefits of this product.
The quantity of Rho(D) antibody in each single-dose
syringe of HyperRHO® Full Dose is equal to or greater
than 1500 IU (300 mcg).
Caution: Rho(D) Immune Globulin (Human) should be
administered to unsensitized Rh negative women
preferably within 3 days after any miscarriage or after
delivery of an Rh positive infant.
GRIFOLS
For complete dosage and administration information, read
enclosed package insert.
For directions for syringe usage, see enclosed package
insert.
Store at 2°C to 8°C (36°F to 46°F). Do not freeze.
Do not use if the syringe is prematurely engaged.
Not made with natural rubber latex.
No preservative
Discard unused portion.
Grifols Therapeutics LLC
Research Triangle Park,
NC 27709 USA
U.S. License No. 1871
GRIFOLS
NDC 13533-631-11
1500 IU (300 mcg)
Rho (D) Immune Globulin (Human)
HyperRHO® Full Dose
Contents: 10 cartons, each with a single-dose
disposable syringe with attached needle
GTIN 00313533631116
LOT XXXXXXXXXX
EXP DDMMMYYYY
SN XXXXXXXXXXXXXXXX